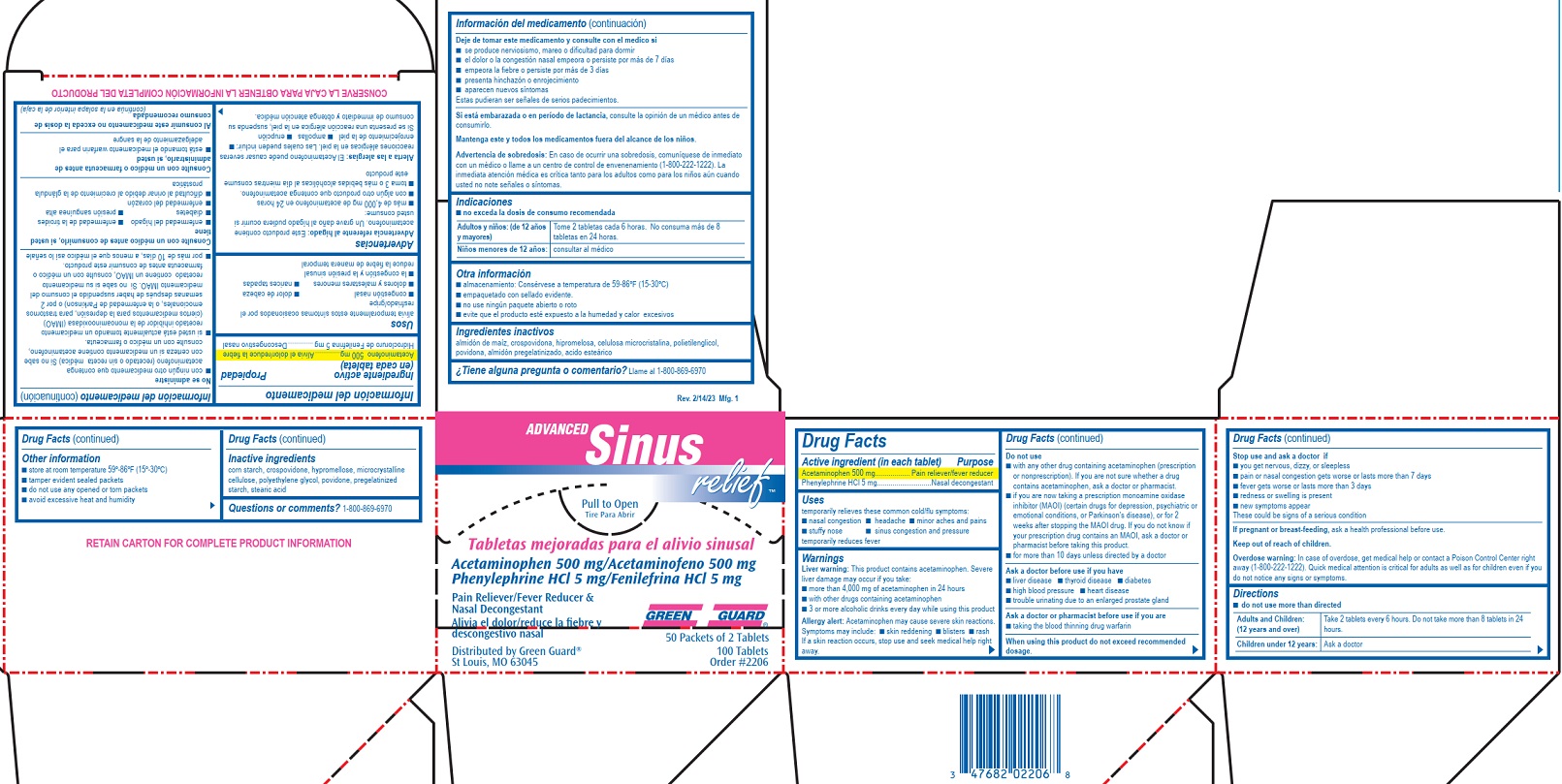 DRUG LABEL: Green Guard Advanced Sinus Relief
NDC: 47682-001 | Form: TABLET
Manufacturer: Unifirst First Aid Corporation
Category: otc | Type: HUMAN OTC DRUG LABEL
Date: 20250908

ACTIVE INGREDIENTS: ACETAMINOPHEN 500 mg/1 1; PHENYLEPHRINE HYDROCHLORIDE 5 mg/1 1
INACTIVE INGREDIENTS: CELLULOSE, MICROCRYSTALLINE; HYPROMELLOSES; POLYETHYLENE GLYCOL, UNSPECIFIED; STARCH, CORN; STEARIC ACID; CROSPOVIDONE; POVIDONE, UNSPECIFIED

819R Green Guard Advanced Sinus Relief

Drug Facts

Active ingredients (in each tablet)

Acetaminophen 500 mg

Phenylephrine HCl 5 mg

Purpose

Pain reliever/fever reducer

Nasal decongestant

Uses

temporarily relieves these common cold/flu symptoms:

- nasal congestion
- headache
- minor aches and pains
- stuffy nose
- sinus congestion and pressure

temporarily reduces fever

Warnings

Liver warning: This product contains acetaminophen. Severe liver damage may occur if you take:

- more than 4,000 mg of acetaminophen in 24 hours
- with other drugs containing acetaminophen
- 3 or more alcoholic drinks every day while using this product

Allergy alert:

Acetaminophen may cause severe skin reactions. Symptoms may include:

- skin reddening
- blisters
- rash

If a skin reaction occurs, stop use and seek medical help right away.

Do not use

- with any other drug containing acetaminophen (prescription or nonprescription). If you are not sure whether a drug contains acetaminophen, ask a doctor or pharmacist.
- if you are now taking a prescription monoamine oxidase inhibitor (MAOI) (certain drugs for depression, psychiatric or emotional conditions, or Parkinson's disease), or for 2 weeks after stopping the MAOI drug. If you do not know if your prescription drug contains an MAOI, ask a doctor or pharmacist before taking this product.
- for more than 10 days unless directed by a doctor

Ask a doctor before use if you have

- liver disease
- thyroid disease
- diabetes
- high blood pressure
- heart disease
- trouble urinating due to an enlarged prostate gland

Ask a doctor or pharmacist before use if you are

- taking the blood thinning drug warfarin

When using this product do not exceed recommended dosage.

Stop use and ask a doctor if

- you get nervous, dizzy, or sleepless
- pain or nasal congestion gets worse or lasts more than 7 days
- fever gets worse or lasts more than 3 days
- redness or swelling is present
- new symptoms appear

These could be signs of a serious condition.

PREGNANCY OR BREAST FEEDING

If pregnant or breast-feeding, ask a health professional before use.

Keep out of reach of children.

Overdose warning:

In case of overdose, get medical help or contact a Poison Control Center right away (1-800-222-1222).

Quick medical attention is critical for adults as well as for children even if you do not notice any signs or symptoms.

Directions

■ do not use more than directed

Adults and children: (12 years and over) Take 2 tablets every 6 hours. Do not take more than 8 tablets in 24 hours.

Children under 12 years: Ask a doctor

Other information

- store at room temperature 59º-86ºF (15º-30ºC)
- tamper evident sealed packets
- do not use any opened or torn packets
- avoid excessive heat and humidity

Inactive ingredients

corn starch, crospovidone, hypromellose, microcrystalline cellulose, polyethylene glycol, povidone, pregelatinized starch, stearic acid.

Questions or comments? 1-800-869-6970

PACKAGE LABEL

Advanced Sinus relief™

Acetaminophen 500mg/Acetaminofeno 500mg

Phenylephrine HCl 5mg/Fenilefrina HCl 5mg

Tabletas mejoradas para el alivio sinusal

Pain Reliever & Fever Reducer & Nasal Decongestant / Alivia el dolor y reduce la fiebre y descongestivo nasal

Pull to Open

Tire Para Abrir

GREEN GUARD ®

50 Packets of 2 Tablets
100 Tablets
Order #2206
Distributed by Green Guard ®, St Louis, MO 63045